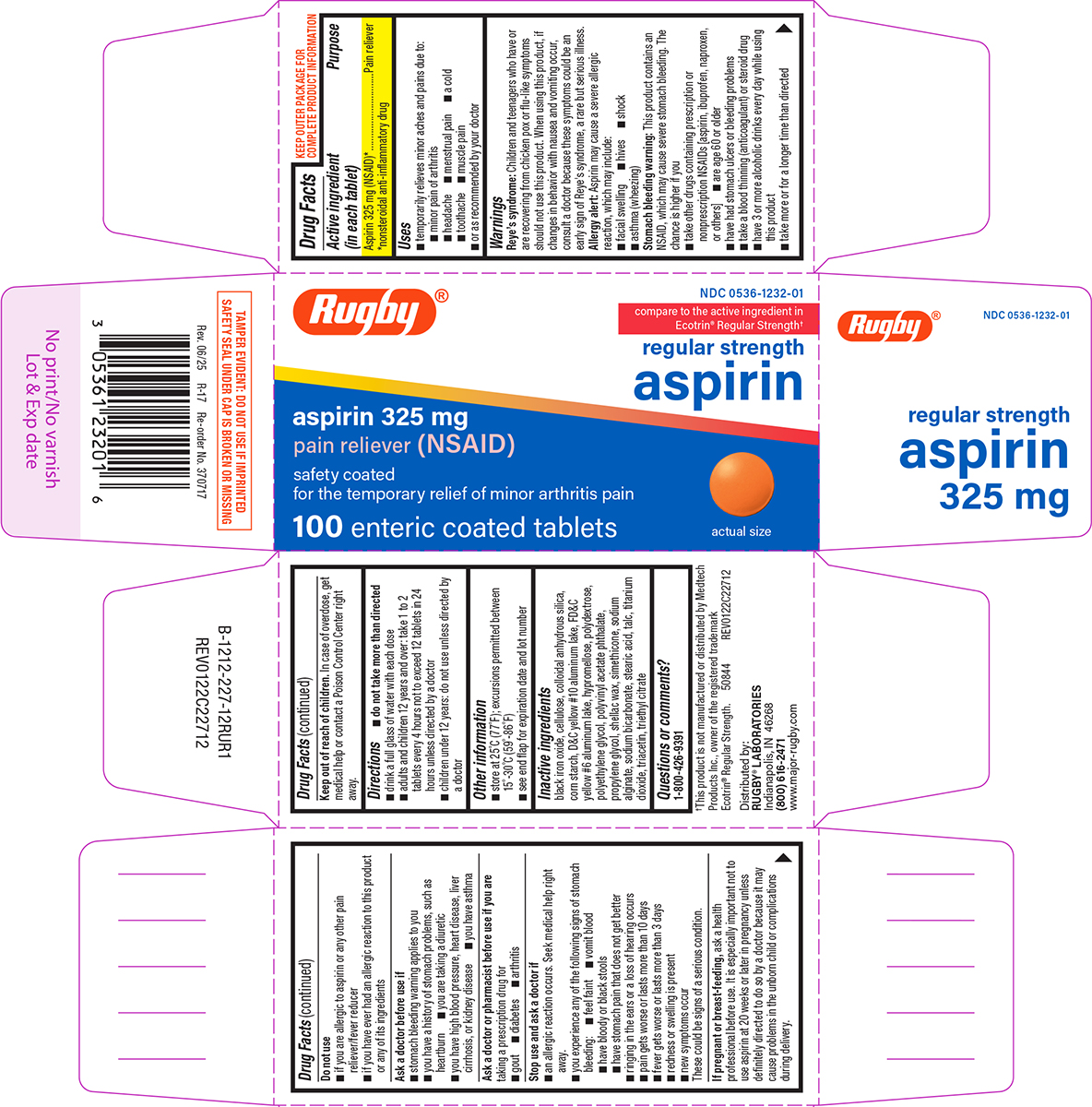 DRUG LABEL: Aspirin
NDC: 0536-1232 | Form: TABLET, DELAYED RELEASE
Manufacturer: Rugby Laboratories
Category: otc | Type: HUMAN OTC DRUG LABEL
Date: 20260204

ACTIVE INGREDIENTS: ASPIRIN 325 mg/1 1
INACTIVE INGREDIENTS: FERROSOFERRIC OXIDE; POWDERED CELLULOSE; SILICON DIOXIDE; STARCH, CORN; D&C YELLOW NO. 10 ALUMINUM LAKE; FD&C YELLOW NO. 6 ALUMINUM LAKE; HYPROMELLOSE, UNSPECIFIED; POLYDEXTROSE; POLYETHYLENE GLYCOL, UNSPECIFIED; Polyvinyl Acetate Phthalate; PROPYLENE GLYCOL; SHELLAC; DIMETHICONE; WATER; SODIUM ALGINATE; SODIUM BICARBONATE; STEARIC ACID; TALC; TITANIUM DIOXIDE; TRIACETIN; TRIETHYL CITRATE

Rugby 44-227

Active ingredient (in each tablet)

Aspirin 325 mg (NSAID)*
*nonsteroidal anti-inflammatory drug

Purpose

Pain reliever

Uses

- temporarily relieves minor aches and pains due to:
  - headache
  - menstrual pain
  - a cold
  - toothache
  - muscle pain
  - minor pain of arthritis
- or as recommended by your doctor

Warnings

Reye’s syndrome: Children and teenagers who have or are recovering from chicken pox or flu-like symptoms should not use this product. When using this product, if changes in behavior with nausea and vomiting occur, consult a doctor because these symptoms could be an early sign of Reye's syndrome, a rare but serious illness.

Allergy alert: Aspirin may cause a severe allergic reaction, which may include:

- facial swelling
- hives
- shock
- asthma (wheezing)

Stomach bleeding warning: This product contains an NSAID, which may cause severe stomach bleeding. The chance is higher if you

- take other drugs containing prescription or nonprescription NSAIDs [aspirin, ibuprofen, naproxen, or others]
- are age 60 or older
- have had stomach ulcers or bleeding problems
- take a blood thinning (anticoagulant) or steroid drug
- take more or for a longer time than directed
- have 3 or more alcoholic drinks every day while using this product

Do not use

- if you are allergic to aspirin or any other pain reliever/fever reducer
- if you have ever had an allergic reaction to this product or any of its ingredients

Ask a doctor before use if

- stomach bleeding warning applies to you
- you have a history of stomach problems, such as heartburn
- you are taking a diuretic
- you have high blood pressure, heart disease, liver cirrhosis, or kidney disease
- you have asthma

Ask a doctor or pharmacist before use if you are

taking a prescription drug for

- diabetes
- arthritis
- gout

Stop use and ask a doctor if

- an allergic reaction occurs. Seek medical help right away.
- you experience any of the following signs of stomach bleeding:
  - vomit blood
  - feel faint
  - have bloody or black stools
  - have stomach pain that does not get better
- ringing in the ears or a loss of hearing occurs
- new symptoms occur
- pain gets worse or lasts more than 10 days
- fever gets worse or lasts more than 3 days
- redness or swelling is present

These could be signs of a serious condition.

If pregnant or breast-feeding,

ask a health professional before use. It is especially important not to use aspirin at 20 weeks or later in pregnancy unless definitely directed to do so by a doctor because it may cause problems in the unborn child or complications during delivery.

Keep out of reach of children.

In case of overdose, get medical help or contact a Poison Control Center right away.

Directions

- do not take more than directed
- drink a full glass of water with each dose
- adults and children 12 years and over: take 1 to 2 tablets every 4 hours while symptoms last
- do not take more than 12 tablets in 24 hours unless directed by a doctor
- children under 12 years: do not use unless directed by a doctor

Other information

- store at 25°C (77°F); excursions permitted between 15°-30°C (59°-86°F)
- see end flap for expiration date and lot number

Inactive ingredients

black iron oxide, cellulose, colloidal anhydrous silica, corn starch, D&C yellow #10 aluminum lake, FD&C yellow #6 aluminum lake, hypromellose, polydextrose, polyethylene glycol, polyvinyl acetate phthalate, propylene glycol, shellac wax, simethicone, sodium alginate, sodium bicarbonate, stearic acid, talc, titanium dioxide, triacetin, triethyl citrate

Questions or comments?

1-800-426-9391

Principal display panel

Rugby®

NDC 0536-1232-01

compare to the active ingredient in
Ecotrin® Regular Strength†

regular strength
aspirin
aspirin 325 mg
pain reliever (NSAID)

safety coated
for the temporary relief of minor arthritis pain

100 enteric coated tablets

actual size

TAMPER EVIDENT: DO NOT USE IF IMPRINTED
SAFETY SEAL UNDER CAP IS BROKEN OR MISSING

†This product is not manufactured or distributed by Medtech
Products Inc., owner of the registered trademark
Ecotrin® Regular Strength. 50844 REV0122C22712

Distributed by:
RUGBY® LABORATORIES
Indianapolis, IN 46268
(800) 616-2471
www.major-rugby.com

Rugby 44-227